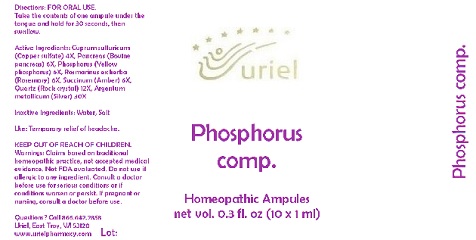 DRUG LABEL: Phosphorus comp.
NDC: 48951-8029 | Form: LIQUID
Manufacturer: Uriel Pharmacy Inc.
Category: homeopathic | Type: HUMAN OTC DRUG LABEL
Date: 20180525

ACTIVE INGREDIENTS: CUPRIC SULFATE 4 [hp_X]/1 mL; SUS SCROFA PANCREAS 6 [hp_X]/1 mL; PHOSPHORUS 6 [hp_X]/1 mL; ROSMARINUS OFFICINALIS FLOWERING TOP 6 [hp_X]/1 mL; AMBER 6 [hp_X]/1 mL; SILICON DIOXIDE 12 [hp_X]/1 mL; SILVER 30 [hp_X]/1 mL
INACTIVE INGREDIENTS: WATER; SODIUM CHLORIDE

Phosphorus comp.

INDICATIONS AND USAGE

Directions: FOR ORAL USE.

DOSAGE AND ADMINISTRATION

Take the contents of one ampule under the tongue and hold for 30 seconds, then swallow.

ACTIVE INGREDIENT

Active Ingredients: Cuprum sulfuricum (Copper sulfate) 4X, Pancreas (Bovine pancreas) 6X, Phosphorus (Yellow phosphorus) 6X, Rosmarinus ex herba (Rosemary) 6X, Succinum (Amber) 6X, Quartz (Rock crystal) 12X, Argentum metallicum (Silver) 30X

Inactive Ingredients: Water, Salt

PURPOSE

Use: Temporary relief of headache.

KEEP OUT OF REACH OF CHILDREN.

WARNINGS

Warnings: Claims based on traditional homeopathic practice, not accepted medical evidence. Not FDA evaluated. Do not use if allergic to any ingredient. Consult a doctor before use for serious conditions or if conditions worsen or persist. If pregnant or nursing, consult a doctor before use.

QUESTIONS

Questions? Call 866.642.2858 Uriel, East Troy, WI 53120 www.urielpharmacy.com